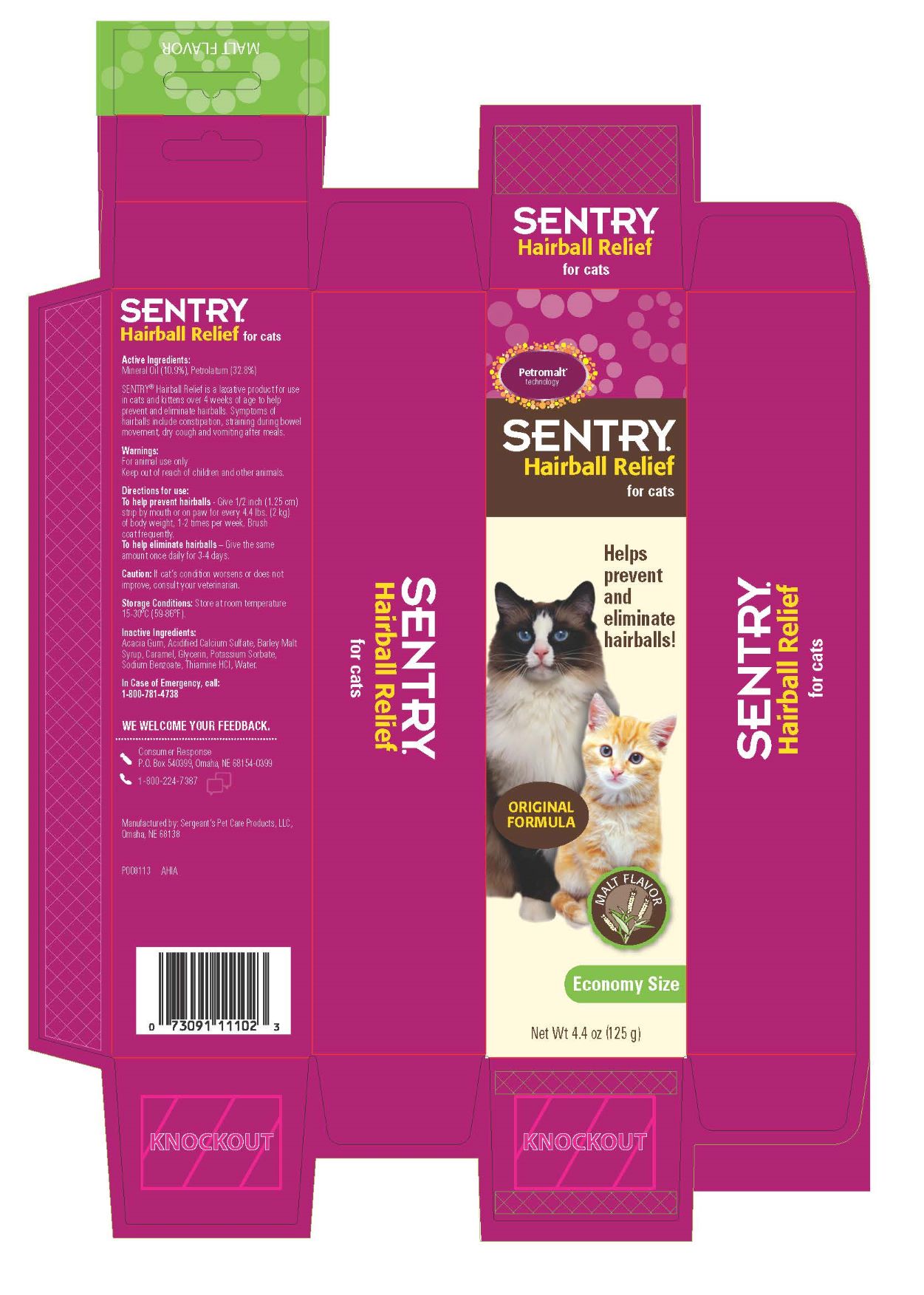 DRUG LABEL: Hairball Relief
NDC: 21091-401 | Form: PASTE
Manufacturer: Sergeant's Pet Care Products LLC
Category: animal | Type: OTC ANIMAL DRUG LABEL
Date: 20231108

ACTIVE INGREDIENTS: MINERAL OIL 6.19 1/1 1; PETROLATUM 18.63 1/1 1
INACTIVE INGREDIENTS: ACACIA 1.20 1/1 1; CALCIUM SULFATE 0.03 1/1 1; BARLEY MALT SYRUP 26.33 1/1 1; CARAMEL 0.30 1/1 1; GLYCERIN 3.95 1/1 1; POTASSIUM SORBATE 0.06 1/1 1; SODIUM BENZOATE 0.06 1/1 1; THIAMINE HYDROCHLORIDE 0.01 1/1 1; WATER 0.06 1/1 1

Active Ingredients:

Mineral Oil (10.9%), Petrolatum (32.8%)

PURPOSE

SENTRY® Hairball Relief is a laxative product for use in cats and kittens over 4 weeks of age to help prevent and eliminate hairballs. Symptoms of hairballs include constipation, straining during bowel movement, dry cough and vomiting after meals.

Warnings:

For animal use only
Keep out of reach of children and other animals.

Directions for use:

To help prevent hairballs - Give 1/2 inch (1.25 cm) strip by mouth or on paw for every 4.4 lbs. (2 kg) of body weight, 1-2 times per week. Brush coat frequently.
To help eliminate hairballs – Give the same amount once daily for 3-4 days.

Caution:

If cat’s condition worsens or does not improve, consult your veterinarian.

Storage Conditions:

Store at room temperature 15-30°C (59-86°F).

Inactive Ingredients:

Acacia Gum, Acidified Calcium Sulfate, Barley Malt Syrup, Caramel, Glycerin, Potassium Sorbate, Sodium Benzoate, Thiamine HCI, Water.

QUESTIONS

In Case of Emergency, call: 1-800-781-4738

WE WELCOME YOUR FEEDBACK.

Consumer Response
P.O. Box 540399, Omaha, NE 68154-0399
1-800-224-7387